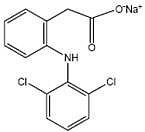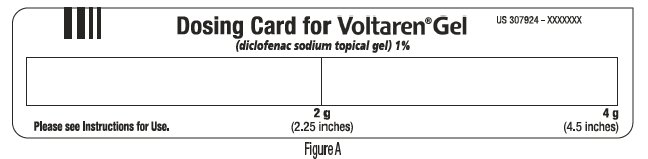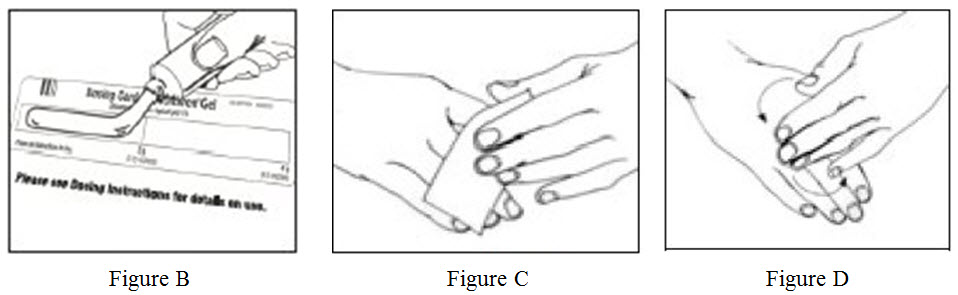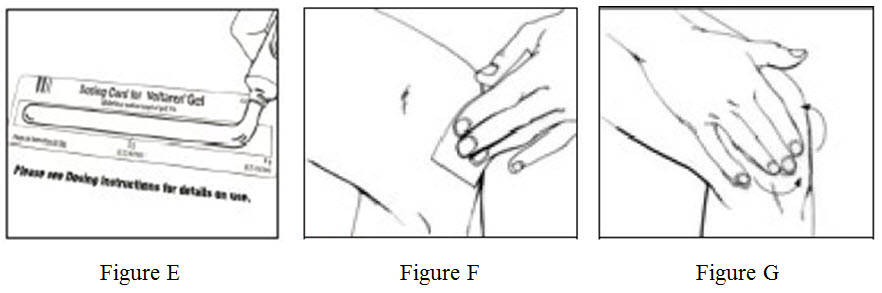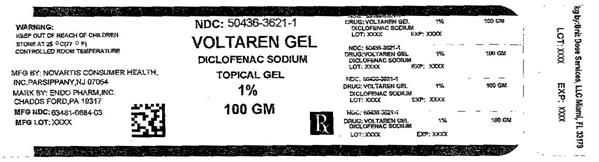 DRUG LABEL: Voltaren
NDC: 50436-3621 | Form: GEL
Manufacturer: Unit Dose Services
Category: prescription | Type: HUMAN PRESCRIPTION DRUG LABEL
Date: 20170828

ACTIVE INGREDIENTS: DICLOFENAC SODIUM 10 mg/1 g
INACTIVE INGREDIENTS: AMMONIA; CARBOMER HOMOPOLYMER TYPE C (ALLYL PENTAERYTHRITOL CROSSLINKED); COCO-CAPRYLATE/CAPRATE; ISOPROPYL ALCOHOL; MINERAL OIL; POLYOXYL 20 CETOSTEARYL ETHER; PROPYLENE GLYCOL; WATER

HIGHLIGHTS OF PRESCRIBING INFORMATION

These highlights do not include all the information needed to use VOLTAREN® GEL safely and effectively. See full prescribing information for VOLTAREN® GEL.
VOLTAREN® GEL (diclofenac sodium topical gel), 1%, for topical use only
Initial U.S. Approval: 1988

RECENT MAJOR CHANGES

Boxed Warning 04/2016

Warnings and Precautions, Cardiovascular Thrombotic Events (5.1) 04/2016

Warnings and Precautions, Heart Failure and Edema (5.5) 04/2016

WARNING: RISK OF SERIOUS CARDIOVASCULAR AND GASTROINTESTINAL EVENTS

See full prescribing information for complete boxed warning.

- Nonsteroidal anti-inflammatory drugs (NSAIDs) cause an increased risk of serious cardiovascular thrombotic events, including myocardial infarction and stroke, which can be fatal. This risk may occur early in treatment and may increase with duration of use. (5.1).
- VOLTAREN® GEL is contraindicated in the setting of coronary artery bypass graft (CABG) surgery. (4, 5.1)
- NSAIDs cause an increased risk of serious gastrointestinal (GI) adverse events including bleeding, ulceration, and perforation of the stomach or intestines, which can be fatal. These events can occur at any time during use and without warning symptoms. Elderly patients and patients with a prior history of peptic ulcer disease and/or GI bleeding are at greater risk for serious GI events. (5.2)

1 INDICATIONS AND USAGE

VOLTAREN® GEL is a non-steroidal anti-inflammatory drug indicated for the relief of the pain of osteoarthritis of joints amenable to topical treatment, such as the knees and those of the hands. (1)

- VOLTAREN® GEL was not evaluated for use on joints of the spine, hip, or shoulder. (14.1)

2 DOSAGE AND ADMINISTRATION

- Use the lowest effective dosage for the shortest duration consistent with individual patient treatment goals (2.1)
- Lower extremities: Apply the gel (4 g) to the affected area 4 times daily. Do not apply more than 16 g daily to any one affected joint of the lower extremities. (2.2)
- Upper extremities: Apply the gel (2 g) to the affected area 4 times daily. Do not apply more than 8 g daily to any one affected joint of the upper extremities. (2.3)
- Total dose should not exceed 32 g per day, over all affected joints. (2.3) VOLTAREN® GEL should be measured onto the enclosed dosing card to the appropriate 2 g or 4 g designation. (2)

3 DOSAGE FORMS AND STRENGTHS

- 1% gel VOLTAREN® GEL (diclofenac sodium topical gel), 1%, (3)

4 CONTRAINDICATIONS

- Known hypersensitivity to diclofenac or any components of the drug product. (4)
- History of asthma, urticaria, or other allergic-type reactions after taking aspirin or other NSAIDs. (4)
- In the setting of CABG surgery. (4)

5 WARNINGS AND PRECAUTIONS

- Hepatotoxicity: Inform patients of warning signs and symptoms of hepatotoxicity. Discontinue if abnormal liver tests persist or worsen or if clinical signs and symptoms of liver disease develop (5.3)
- Hypertension: Patients taking some antihypertensive medications may have impaired response to these therapies when taking NSAIDs. Monitor blood pressure (5.4, 7)
- Heart Failure and Edema: Avoid use of VOLTAREN® GEL in patients with severe heart failure unless benefits are expected to outweigh risk of worsening heart failure (5.5)
- Renal Toxicity: Monitor renal function in patients with renal or hepatic impairment, heart failure, dehydration, or hypovolemia. Avoid use of VOLTAREN® GEL in patients with advanced renal disease unless benefits are expected to outweigh risk of worsening renal function (5.6)
- Anaphylactic Reactions: Seek emergency help if an anaphylactic reaction occurs (5.7)
- Exacerbation of Asthma Related to Aspirin Sensitivity: VOLTAREN® GEL is contraindicated in patients with aspirin-sensitive asthma. Monitor patients with preexisting asthma (without aspirin sensitivity) (5.8)
- Serious Skin Reactions: Discontinue VOLTAREN® GEL at first appearance of rash or other signs of hypersensitivity (5.9)
- Premature Closure of Fetal Ductus Arteriosus: Avoid use in pregnant women starting at 30 weeks gestation. (5.10, 8.1)
- Hematologic Toxicity: Monitor hemoglobin or hematocrit in patients with any signs or symptoms of anemia (5.11, 7)

6 ADVERSE REACTIONS

Most common adverse reactions (incidence >2% of patients treated with VOLTAREN® GEL and greater than placebo) are application site reactions, including dermatitis. (6.1)

To report SUSPECTED ADVERSE REACTIONS, contact Sandoz Inc. at 1-800-525-8747 or FDA at 1-800-FDA-1088 or www.fda.gov/medwatch

7 DRUG INTERACTIONS

- Drugs that Interfere with Hemostasis (e.g. warfarin, aspirin, SSRIs/SNRIs): Monitor patients for bleeding who are concomitantly using VOLTAREN® GEL with drugs that interfere with hemostasis. Concomitant use of VOLTAREN® GEL and analgesic doses of aspirin is not generally recommended (7)
- ACE Inhibitors, Angiotensin Receptor Blockers (ARB), or Beta-Blockers: Concomitant use with VOLTAREN® GEL may diminish the antihypertensive effect of these drugs. Monitor blood pressure (7)
- ACE Inhibitors and ARBs: Concomitant use with VOLTAREN® GEL in elderly, volume depleted, or those with renal impairment may result in deterioration of renal function. In such high risk patients, monitor for signs of worsening renal function (7)
- Diuretics: NSAIDs can reduce natriuretic effect of furosemide and thiazide diuretics. Monitor patients to assure diuretic efficacy including antihypertensive effects (7)
- Digoxin: Concomitant use with VOLTAREN® GEL can increase serum concentration and prolong half-life of digoxin. Monitor serum digoxin levels (7)

8 USE IN SPECIFIC POPULATIONS

Pregnancy: Use of NSAIDs during the third trimester of pregnancy increases the risk of premature closure of the fetal ductus arteriosus. Avoid use of NSAIDs in pregnant women starting at 30 weeks gestation (5.10, 8.1)

Infertility: NSAIDs are associated with reversible infertility. Consider withdrawal of VOLTAREN® GEL in women who have difficulties conceiving. (8.3)

FULL PRESCRIBING INFORMATION

WARNING: RISK OF SERIOUS CARDIOVASCULAR AND GASTROINTESTINAL EVENTS

Cardiovascular Thrombotic Events

- Nonsteroidal anti-inflammatory drugs (NSAIDs) cause an increased risk of serious cardiovascular thrombotic events, including myocardial infarction and stroke, which can be fatal. This risk may occur early in treatment and may increase with duration of use [see Warnings and Precautions (5.1)].
- VOLTAREN® GEL is contraindicated in the setting of coronary artery bypass graft (CABG) surgery [see Contraindications (4) and Warnings and Precautions (5.1)].

Gastrointestinal Bleeding, Ulceration, and Perforation

- NSAIDs cause an increased risk of serious gastrointestinal (GI) adverse events including bleeding, ulceration, and perforation of the stomach or intestines, which can be fatal. These events can occur at any time during use and without warning symptoms. Elderly patients and patients with a prior history of peptic ulcer disease and/or GI bleeding are at greater risk for serious GI events [see Warnings and Precautions (5.2)].

1 INDICATIONS AND USAGE

VOLTAREN® GEL is indicated for the relief of the pain of osteoarthritis of joints amenable to topical treatment, such as the knees and those of the hands.

- VOLTAREN® GEL has not been evaluated for use on the spine, hip, or shoulder.

2 DOSAGE AND ADMINISTRATION

Use the lowest effective dosage for the shortest duration consistent with individual patient treatment goals [see Warnings and Precautions (5)].

2.1 Dosing Card

[See the Patient Instructions for Use]

The dosing card can be found attached to the inside of the carton.

The proper amount of VOLTAREN® GEL should be measured using the dosing card supplied in the drug product carton. The dosing card is made of clear polypropylene. The dosing card should be used for each application of drug product. The gel should be applied within the rectangular area of the dosing card up to the 2 gram or 4 gram line (2 g for each elbow, wrist, or hand, and 4 g for each knee, ankle, or foot). The 2 g line is 2.25 inches long. The 4 g line is 4.5 inches long. The dosing card containing VOLTAREN® GEL can be used to apply the gel. The hands should then be used to gently rub the gel into the skin. After using the dosing card, hold with fingertips, rinse, and dry. If treatment site is the hands, patients should wait at least one (1) hour to wash their hands.

2.2 Lower extremities, including the feet, ankles, or knees

Apply the gel (4 g) to the affected foot, ankle, or knee 4 times daily. VOLTAREN® GEL should be gently massaged into the skin ensuring application to the entire affected foot, or knee or ankle. The entire foot includes the sole, top of the foot and the toes. Do not apply more than 16 g daily to any single joint of the lower extremities.

2.3 Upper extremities including the hands, wrists, or elbows

Apply the gel (2 g) to the affected hand, wrist, or elbow 4 times daily. VOLTAREN® GEL should be gently massaged into the skin ensuring application to the entire affected hand, wrist, or elbow. The entire hand includes the palm, back of the hands, and the fingers. Do not apply more than 8 g daily to any single joint of the upper extremities.

Total dose should not exceed 32 g per day, over all affected joints.

2.4 Special Precautions

- Avoid showering/bathing for at least 1 hour after the application. Inform patient to wash his/her hands after use, unless the hands are the treated joint. If VOLTAREN® GEL is applied to the hand(s) for treatment; inform patient not to wash the treated hand(s) for at least 1 hour after the application.
- Do not apply VOLTAREN® GEL to open wounds.
- Avoid contact of VOLTAREN® GEL with eyes and mucous membranes.
- Do not apply external heat and/or occlusive dressings to treated joints.
- Avoid exposure of the treated joint(s) to natural or artificial sunlight.
- Avoid concomitant use of VOLTAREN® GEL on the treated skin site with other topical products, including sunscreens, cosmetics, lotions, moisturizers, insect repellants, or other topical medications.
- Concomitant use of VOLTAREN® GEL with oral non-steroidal anti-inflammatory drugs (NSAIDs) has not been evaluated, and may increase adverse NSAIDs effects. Do not use combination therapy with VOLTAREN® GEL and an oral NSAID unless the benefit outweighs the risk and conduct periodic laboratory evaluations.
- Avoid wearing of clothing or gloves for at least 10 minutes after applying VOLTAREN® GEL.

3 DOSAGE FORMS AND STRENGTHS

VOLTAREN® GEL (diclofenac sodium topical gel), 1%

4 CONTRAINDICATIONS

VOLTAREN® GEL is contraindicated in the following patients:

- Known hypersensitivity (e.g., anaphylactic reactions and serious skin reactions) to diclofenac or any components of the drug product [see Warnings and Precautions (5.7, 5.9)]
- History of asthma, urticaria, or other allergic-type reactions after taking aspirin or other NSAIDs. Severe, sometimes fatal, anaphylactic reactions to NSAIDs have been reported in such patients [see Warnings and Precautions (5.7, 5.8)]
- In the setting of coronary artery bypass graft (CABG) surgery [see Warnings and Precautions (5.1)].

5 WARNINGS AND PRECAUTIONS

5.1 Cardiovascular Thrombotic Events

Clinical trials of several COX-2 selective and nonselective NSAIDs of up to three years duration have shown an increased risk of serious cardiovascular (CV) thrombotic events, including myocardial infarction (MI) and stroke, which can be fatal. Based on available data, it is unclear that the risk for CV thrombotic events is similar for all NSAIDs. The relative increase in serious CV thrombotic events over baseline conferred by NSAID use appears to be similar in those with and without known CV disease or risk factors for CV disease. However, patients with known CV disease or risk factors had a higher absolute incidence of excess serious CV thrombotic events, due to their increased baseline rate. Some observational studies found that this increased risk of serious CV thrombotic events began as early as the first weeks of treatment. The increase in CV thrombotic risk has been observed most consistently at higher doses.

To minimize the potential risk for an adverse CV event in NSAID-treated patients, use the lowest effective dose for the shortest duration possible. Physicians and patients should remain alert for the development of such events, throughout the entire treatment course, even in the absence of previous CV symptoms. Patients should be informed about the symptoms of serious CV events and the steps to take if they occur.

There is no consistent evidence that concurrent use of aspirin mitigates the increased risk of serious CV thrombotic events associated with NSAID use. The concurrent use of aspirin and an NSAID, such as diclofenac, increases the risk of serious gastrointestinal (GI) events [see Warnings and Precautions (5.2)].

Status Post Coronary Artery Bypass Graft (CABG) Surgery

Two large, controlled clinical trials of a COX-2 selective NSAID for the treatment of pain in the first 10-14 days following CABG surgery found an increased incidence of myocardial infarction and stroke. NSAIDs are contraindicated in the setting of CABG [see Contraindications (4)].

Post-MI Patients

Observational studies conducted in the Danish National Registry have demonstrated that patients treated with NSAIDs in the post-MI period were at increased risk of reinfarction, CV-related death, and all-cause mortality beginning in the first week of treatment. In this same cohort, the incidence of death in the first year post-MI was 20 per 100 person years in NSAID-treated patients compared to 12 per 100 person years in non-NSAID exposed patients. Although the absolute rate of death declined somewhat after the first year post-MI, the increased relative risk of death in NSAID users persisted over at least the next four years of follow-up.

Avoid the use of VOLTAREN® GEL in patients with a recent MI unless the benefits are expected to outweigh the risk of recurrent CV thrombotic events. If VOLTAREN® GEL is used in patients with a recent MI, monitor patients for signs of cardiac ischemia.

5.2 Gastrointestinal Bleeding, Ulceration, and Perforation

NSAIDs, including diclofenac, cause serious gastrointestinal (GI) adverse events including inflammation, bleeding, ulceration, and perforation of the esophagus, stomach, small intestine, or large intestine, which can be fatal. These serious adverse events can occur at any time, with or without warning symptoms, in patients treated with NSAIDs. Only one in five patients who develop a serious upper GI adverse event on NSAID therapy is symptomatic. Upper GI ulcers, gross bleeding, or perforation caused by NSAIDs occurred in approximately 1% of patients treated for 3-6 months, and in about 2%-4% of patients treated for one year. However, even short-term NSAID therapy is not without risk.

Risk Factors for GI Bleeding, Ulceration, and Perforation

Patients with a prior history of peptic ulcer disease and/or GI bleeding who used NSAIDs had a greater than 10-fold increased risk for developing a GI bleed compared to patients without these risk factors. Other factors that increase the risk of GI bleeding in patients treated with NSAIDs include longer duration of NSAID therapy; concomitant use of oral corticosteroids, aspirin, anticoagulants, or selective serotonin reuptake inhibitors (SSRIs); smoking; use of alcohol; older age; and poor general health status. Most postmarketing reports of fatal GI events occurred in elderly or debilitated patients. Additionally, patients with advanced liver disease and/or coagulopathy are at increased risk for GI bleeding.

Strategies to Minimize the GI Risks in NSAID-treated patients:

- Use the lowest effective dosage for the shortest possible duration.
- Avoid administration of more than one NSAID at a time.
- Avoid use in patients at higher risk unless benefits are expected to outweigh the increased risk of bleeding. For such patients, as well as those with active GI bleeding, consider alternate therapies other than NSAIDs.
- Remain alert for signs and symptoms of GI ulceration and bleeding during NSAID therapy.
- If a serious GI adverse event is suspected, promptly initiate evaluation and treatment, and discontinue VOLTAREN® GEL until a serious GI adverse event is ruled out.
- In the setting of concomitant use of low-dose aspirin for cardiac prophylaxis, monitor patients more closely for evidence of GI bleeding [see Drug Interactions (7)].

5.3 Hepatotoxicity

In clinical trials, of oral diclofenac-containing products, meaningful elevations (i.e., more than 3 times the ULN) of AST (SGOT) were observed in about 2% of approximately 5,700 patients at some time during diclofenac treatment (ALT was not measured in all studies).

In a large, open-label, controlled trial of 3,700 patients treated with oral diclofenac sodium for 2-6 months, patients were monitored first at 8 weeks and 1,200 patients were monitored again at 24 weeks. Meaningful elevations of ALT and/or AST occurred in about 4% of 3,700 patients and included marked elevations (greater than 8 times the ULN) in about 1% of the 3,700 patients. In that open-label study, a higher incidence of borderline (less than 3 times the ULN), moderate (3-8 times the ULN), and marked (greater than 8 times the ULN) elevations of ALT or AST was observed in patients receiving diclofenac when compared to other NSAIDs. Elevations in transaminases were seen more frequently in patients with osteoarthritis than in those with rheumatoid arthritis.

Almost all meaningful elevations in transaminases were detected before patients became symptomatic. Abnormal tests occurred during the first 2 months of therapy with diclofenac in 42 of the 51 patients in all trials who developed marked transaminase elevations.

In postmarketing reports, cases of drug-induced hepatotoxicity have been reported in the first month, and in some cases, the first 2 months of therapy, but can occur at any time during treatment with diclofenac. Postmarketing surveillance has reported cases of severe hepatic reactions, including liver necrosis, jaundice, fulminant hepatitis with and without jaundice, and liver failure. Some of these reported cases resulted in fatalities or liver transplantation.

In a European retrospective population-based, case-controlled study, 10 cases of diclofenac associated drug-induced liver injury with current use compared with non-use of diclofenac were associated with a statistically significant 4-fold adjusted odds ratio of liver injury. In this particular study, based on an overall number of 10 cases of liver injury associated with diclofenac, the adjusted odds ratio increased further with female gender, doses of 150 mg or more, and duration of use for more than 90 days.

Physicians should measure transaminases at baseline and periodically in patients receiving long-term therapy with diclofenac, because severe hepatotoxicity may develop without a prodrome of distinguishing symptoms. The optimum times for making the first and subsequent transaminase measurements are not known. Based on clinical trial data and postmarketing experiences, transaminases should be monitored within 4 to 8 weeks after initiating treatment with diclofenac. However, severe hepatic reactions can occur at any time during treatment with diclofenac.

If abnormal liver tests persist or worsen, if clinical signs and/or symptoms consistent with liver disease develop, or if systemic manifestations occur (e.g., eosinophilia, rash, abdominal pain, diarrhea, dark urine, etc.),VOLTAREN® GEL should be discontinued immediately.

Inform patients of the warning signs and symptoms of hepatotoxicity (e.g., nausea, fatigue, lethargy, diarrhea, pruritus, jaundice, right upper quadrant tenderness, and "flu-like" symptoms). If clinical signs and symptoms consistent with liver disease develop, or if systemic manifestations occur (e.g., eosinophilia, rash, etc.), discontinue VOLTAREN® GEL immediately, and perform a clinical evaluation of the patient.

To minimize the potential risk for an adverse liver related event in patients treated with VOLTAREN® GEL, use the lowest effective dose for the shortest duration possible. Exercise caution when prescribing VOLTAREN® GEL with concomitant drugs that are known to be potentially hepatotoxic (e.g., acetaminophen, antibiotics, anti-epileptics).

5.4 Hypertension

NSAIDs, including VOLTAREN® GEL, can lead to new onset of hypertension or worsening of preexisting hypertension, either of which may contribute to the increased incidence of CV events. Patients taking angiotensin converting enzyme (ACE) inhibitors, thiazide diuretics, or loop diuretics may have impaired response to these therapies when taking NSAIDs [see Drug Interactions (7)].

Monitor blood pressure (BP) during the initiation of NSAID treatment and throughout the course of therapy.

5.5 Heart Failure and Edema

The Coxib and traditional NSAID Trialists’ Collaboration meta-analysis of randomized controlled trials demonstrated an approximately two-fold increase in hospitalizations for heart failure in COX-2 selective-treated patients and nonselective NSAID-treated patients compared to placebo-treated patients. In a Danish National Registry study of patients with heart failure, NSAID use increased the risk of MI, hospitalization for heart failure, and death.

Additionally, fluid retention and edema have been observed in some patients treated with NSAIDs. Use of diclofenac may blunt the CV effects of several therapeutic agents used to treat these medical conditions (e.g., diuretics, ACE inhibitors, or angiotensin receptor blockers [ARBs]) [see Drug interactions (7)].

Avoid the use of VOLTAREN® GEL in patients with severe heart failure unless the benefits are expected to outweigh the risk of worsening heart failure. If VOLTAREN® GEL is used in patients with severe heart failure, monitor patients for signs of worsening heart failure.

5.6 Renal Toxicity and Hyperkalemia

Renal Toxicity

Long-term administration of NSAIDs has resulted in renal papillary necrosis and other renal injury.

Renal toxicity has also been seen in patients in whom renal prostaglandins have a compensatory role in the maintenance of renal perfusion. In these patients, administration of an NSAID may cause a dose-dependent reduction in prostaglandin formation and, secondarily, in renal blood flow, which may precipitate overt renal decompensation. Patients at greatest risk of this reaction are those with impaired renal function, dehydration, hypovolemia, heart failure, liver dysfunction, those taking diuretics and ACE-inhibitors or ARBs, and the elderly. Discontinuation of NSAID therapy is usually followed by recovery to the pretreatment state.

No information is available from controlled clinical studies regarding the use of VOLTAREN® GEL in patients with advanced renal disease. The renal effects of VOLTAREN® GEL may hasten the progression of renal dysfunction in patients with preexisting renal disease.

Correct volume status in dehydrated or hypovolemic patients prior to initiating VOLTAREN® GEL. Monitor renal function in patients with renal or hepatic impairment, heart failure, dehydration, or hypovolemia during use of VOLTAREN® GEL [see Drug Interactions (7)]. Avoid the use of VOLTAREN® GEL in patients with advanced renal disease unless the benefits are expected to outweigh the risk of worsening renal function. If VOLTAREN® GEL is used in patients with advanced renal disease, monitor patients for signs of worsening renal function.

Hyperkalemia

Increases in serum potassium concentration, including hyperkalemia, have been reported with use of NSAIDs, even in some patients without renal impairment. In patients with normal renal function, these effects have been attributed to a hyporeninemic-hypoaldosteronism state.

5.7 Anaphylactoid Reactions

Diclofenac has been associated with anaphylactic reactions in patients with and without known hypersensitivity to diclofenac and in patients with aspirin-sensitive asthma [see Contraindications (4) and Warnings and Precautions (5.8)].

Seek emergency help if an anaphylactic reaction occurs.

5.8 Exacerbation of Asthma Related to Aspirin Sensitivity

A subpopulation of patients with asthma may have aspirin-sensitive asthma which may include chronic rhinosinusitis complicated by nasal polyps; severe, potentially fatal bronchospasm; and/or intolerance to aspirin and other NSAIDs. Because cross-reactivity between aspirin and other NSAIDs has been reported in such aspirin-sensitive patients, VOLTAREN® GEL is contraindicated in patients with this form of aspirin sensitivity [see Contraindications (4)]. When VOLTAREN® GEL is used in patients with preexisting asthma (without known aspirin sensitivity), monitor patients for changes in the signs and symptoms of asthma.

5.9 Serious Skin Reactions

NSAIDs, including diclofenac, can cause serious skin adverse reactions such as exfoliative dermatitis, Stevens-Johnson Syndrome (SJS), and toxic epidermal necrolysis (TEN), which can be fatal. These serious events may occur without warning. Inform patients about the signs and symptoms of serious skin reactions, and to discontinue the use of VOLTAREN® GEL at the first appearance of skin rash or any other sign of hypersensitivity. VOLTAREN® GEL is contraindicated in patients with previous serious skin reactions to NSAIDs [see Contraindications (4)].

5.10 Premature Closure of Fetal Ductus Arteriosus

Diclofenac may cause premature closure of the fetal ductus arteriosus. Avoid use of NSAIDs, including VOLTAREN® GEL, in pregnant women starting at 30 weeks of gestation (third trimester) [see Use in Specific Populations (8.1)].

5.11 Hematologic Toxicity

Anemia has occurred in NSAID-treated patients. This may be due to occult or gross blood loss, fluid retention, or an incompletely described effect on erythropoiesis. If a patient treated with VOLTAREN® GEL has any signs or symptoms of anemia, monitor hemoglobin or hematocrit.

NSAIDs, including VOLTAREN® GEL, may increase the risk of bleeding events. Co-morbid conditions such as coagulation disorders, concomitant use of warfarin, other anticoagulants, antiplatelet agents (e.g., aspirin), serotonin reuptake inhibitors (SSRIs) and serotonin norepinephrine reuptake inhibitors (SNRIs) may increase this risk. Monitor these patients for signs of bleeding [see Drug Interactions (7)].

5.12 Masking of Inflammation and Fever

The pharmacological activity of VOLTAREN® GEL in reducing inflammation, and possibly fever, may diminish the utility of diagnostic signs in detecting infections.

5.13 Laboratory Monitoring

Because serious GI bleeding, hepatotoxicity, and renal injury can occur without warning symptoms or signs, consider monitoring patients on long-term NSAID treatment with a CBC and a chemistry profile periodically [see Warnings and Precautions (5.2, 5.3, 5.6)].

5.14 Sun Exposure

Patients should minimize or avoid exposure to natural or artificial sunlight on treated areas because studies in animals indicated topical diclofenac treatment resulted in an earlier onset of ultraviolet light induced skin tumors. The potential effects of VOLTAREN® GEL on skin response to ultraviolet damage in humans are not known.

5.15 Eye Exposure

Contact of VOLTAREN® GEL with eyes and mucosa, although not studied, should be avoided. Patients should be advised that if eye contact occurs, they should immediately wash out the eye with water or saline and consult a physician if irritation persists for more than an hour.

5.16 Oral Nonsteroidal Anti-Inflammatory Drugs

Concomitant use of oral and topical NSAIDs may result in a higher rate of hemorrhage, more frequent abnormal creatinine, urea and hemoglobin. Do not use combination therapy with VOLTAREN® GEL and an oral NSAID unless the benefit outweighs the risk.

6 ADVERSE REACTIONS

The following adverse reactions are discussed in greater detail in other sections of the labeling:

- Cardiovascular Thrombotic Events [see Warnings and Precautions (5.1)]
- GI Bleeding, Ulceration and Perforation [see Warnings and Precautions (5.2)]
- Hepatotoxicity [see Warnings and Precautions (5.3)]
- Hypertension [see Warnings and Precautions (5.4)]
- Heart Failure and Edema [see Warnings and Precautions (5.5)]
- Renal Toxicity and Hyperkalemia [see Warnings and Precautions (5.6)]
- Anaphylactic Reactions [see Warnings and Precautions (5.7)]
- Serious Skin Reactions [see Warnings and Precautions (5.9)]
- Hematologic Toxicity [see Warnings and Precautions (5.11)]

6.1 Clinical Trials Experience

Because clinical trials are conducted under widely varying conditions, adverse reaction rates observed in the clinical trials of a drug cannot be directly compared with rates in the clinical trials of another drug and may not reflect the rates observed in practice.

During clinical development, 913 patients were exposed to VOLTAREN® GEL in randomized, double-blind, multicenter, vehicle-controlled, parallel-group studies in osteoarthritis of the superficial joints of the extremities. Of these, 513 patients received VOLTAREN® GEL for osteoarthritis of the knee and 400 were treated for osteoarthritis of the hand. Additionally, 583 patients were exposed to VOLTAREN® GEL in an uncontrolled, open-label, long-term safety trial in osteoarthritis of the knee. Of these, 355 patients were treated for osteoarthritis of 1 knee and 228 were treated for osteoarthritis of both knees. Duration of exposure ranged from 8 to 12 weeks for the placebo-controlled studies, and up to 12 months for the open-label safety trial.

Short-Term Placebo-Controlled Trials:
Adverse reactions observed in at least 1% of patients treated with VOLTAREN® GEL: Non-serious adverse reactions that were reported during the short-term placebo-controlled studies comparing VOLTAREN® GEL and placebo (vehicle gel) over study periods of 8 to 12 weeks (16 g per day), were application site reactions. These were the only adverse reactions that occurred in >1% of treated patients with a greater frequency in the VOLTAREN® GEL group (7%) than the placebo group (2%).
Table 1 lists the types of application site reactions reported. Application site dermatitis was the most frequent type of application site reaction and was reported by 4% of patients treated with VOLTAREN® GEL, compared to 1% of placebo patients.

Table 1: Non-serious Application Site Adverse Reactions (≥1% VOLTAREN® GEL Patients) – Short-term Controlled Trials
Adverse Reaction† | VOLTAREN® GEL N=913 | Placebo (vehicle) N=876
Adverse Reaction† | N (%) | N (%)
Any application site reaction | 62 (7) | 19 (2)
Application site dermatitis | 32 (4) | 6 (<1)
Application site pruritus | 7 (<1) | 1 (<1)
Application site erythema | 6 (<1) | 3 (<1)
Application site paresthesia | 5 (<1) | 3 (<1)
Application site dryness | 4 (<1) | 3 (<1)
Application site vesicles | 3 (<1) | 0
Application site irritation | 2 (<1) | 0
Application site papules | 1 (<1) | 0

†Preferred Term according to MedDRA 9.1.

In the placebo-controlled trials, the discontinuation rate due to adverse reactions was 5% for patients treated with VOLTAREN® GEL, and 3% for patients in the placebo group. Application site reactions, including application site dermatitis, were the most frequent reason for treatment discontinuation.

Long-Term Open-Label Safety Trial:
In the open-label, long-term safety study, distribution of adverse reactions was similar to that in the placebo-controlled studies. In this study, where patients were treated for up to 1 year with VOLTAREN® GEL up to 32 g per day, application site dermatitis was observed in 11% of patients. Adverse reactions that led to the discontinuation of the study drug were experienced in 12% of patients. The most common adverse reaction that led to discontinuation of the study was application site dermatitis, which was experienced by 6% of patients.

7 DRUG INTERACTIONS

See Table 2 for clinically significant drug interactions with diclofenac.

Table 2: Clinically Significant Drug Interactions with Diclofenac

Drugs That Interfere with Hemostasis
Clinical Impact: |  | • Diclofenac and anticoagulants such as warfarin have a synergistic effect on bleeding. The concomitant use of diclofenac and anticoagulants have an increased risk of serious bleeding compared to the use of either drug alone. • Serotonin release by platelets plays an important role in hemostasis. Case-control and cohort epidemiological studies showed that concomitant use of drugs that interfere with serotonin reuptake and an NSAID may potentiate the risk of bleeding more than an NSAID alone.
Intervention: |  | Monitor patients with concomitant use of VOLTAREN® GEL with anticoagulants (e.g., warfarin), antiplatelet agents (e.g., aspirin), selective serotonin reuptake inhibitors (SSRIs), and serotonin norepinephrine reuptake inhibitors (SNRIs) for signs of bleeding [see Warnings and Precautions (5.11)].
Aspirin
Clinical Impact: |  | Controlled clinical studies showed that the concomitant use of NSAIDs and analgesic doses of aspirin does not produce any greater therapeutic effect than the use of NSAIDs alone. In a clinical study, the concomitant use of an NSAID and aspirin was associated with a significantly increased incidence of GI adverse reactions as compared to use of the NSAID alone [see Warnings and Precautions (5.2)].
Intervention: |  | Concomitant use of VOLTAREN® GEL and analgesic doses of aspirin is not generally recommended because of the increased risk of bleeding [see Warnings and Precautions (5.11)]. VOLTAREN® GEL is not a substitute for low dose aspirin for cardiovascular protection.
ACE Inhibitors, Angiotensin Receptor Blockers, and Beta-Blockers
Clinical Impact: |  | • NSAIDs may diminish the antihypertensive effect of angiotensin converting enzyme (ACE) inhibitors, angiotensin receptor blockers (ARBs), or beta-blockers (including propranolol). • In patients who are elderly, volume-depleted (including those on diuretic therapy), or have renal impairment, co-administration of an NSAID with ACE inhibitors or ARBs may result in deterioration of renal function, including possible acute renal failure. These effects are usually reversible.
Intervention: |  | • During concomitant use of VOLTAREN® GEL and ACE-inhibitors, ARBs, or beta- blockers, monitor blood pressure to ensure that the desired blood pressure is obtained. • During concomitant use of VOLTAREN® GEL and ACE-inhibitors or ARBs in patients who are elderly, volume-depleted, or have impaired renal function, monitor for signs of worsening renal function [see Warnings and Precautions (5.6)]. - When these drugs are administered concomitantly, patients should be adequately hydrated. Assess renal function at the beginning of the concomitant treatment and periodically thereafter.
Diuretics
Clinical Impact: |  | Clinical studies, as well as post-marketing observations, showed that NSAIDs reduced the natriuretic effect of loop diuretics (e.g., furosemide) and thiazide diuretics in some patients. This effect has been attributed to the NSAID inhibition of renal prostaglandin synthesis.
Intervention: |  | During concomitant use of VOLTAREN® GEL with diuretics, observe patients for signs of worsening renal function, in addition to assuring diuretic efficacy including antihypertensive effects [see Warnings and Precautions (5.6)].
Digoxin
Clinical Impact: |  | The concomitant use of diclofenac with digoxin has been reported to increase the serum concentration and prolong the half-life of digoxin.
Intervention: |  | During concomitant use of VOLTAREN® GEL and digoxin, monitor serum digoxin levels.
Lithium
Clinical Impact: |  | NSAIDs have produced elevations in plasma lithium levels and reductions in renal lithium clearance. The mean minimum lithium concentration increased 15%, and the renal clearance decreased by approximately 20%. This effect has been attributed to NSAID inhibition of renal prostaglandin synthesis.
Intervention: |  | During concomitant use of VOLTAREN® GEL and lithium, monitor patients for signs of lithium toxicity.
Methotrexate
Clinical Impact: |  | Concomitant use of NSAIDs and methotrexate may increase the risk for methotrexate toxicity (e.g., neutropenia, thrombocytopenia, renal dysfunction).
Intervention: |  | During concomitant use of VOLTAREN® GEL and methotrexate, monitor patients for methotrexate toxicity.
Cyclosporine
Clinical Impact: |  | Concomitant use of VOLTAREN® GEL and cyclosporine may increase cyclosporine's nephrotoxicity.
Intervention: |  | During concomitant use of VOLTAREN® GEL and cyclosporine, monitor patients for signs of worsening renal function.
NSAIDs and Salicylates
Clinical Impact: |  | Concomitant use of diclofenac with other NSAIDs or salicylates (e.g., diflunisal, salsalate) increases the risk of GI toxicity, with little or no increase in efficacy [see Warnings and Precautions (5.2)].
Intervention: |  | The concomitant use of diclofenac with other NSAIDs or salicylates is not recommended.
Pemetrexed
Clinical Impact: |  | Concomitant use of VOLTAREN® GEL and pemetrexed may increase the risk of pemetrexed-associated myelosuppression, renal, and GI toxicity (see the pemetrexed prescribing information).
Intervention: |  | During concomitant use of VOLTAREN® GEL and pemetrexed, in patients with renal impairment whose creatinine clearance ranges from 45 to 79 mL/min, monitor for myelosuppression, renal and Gl toxicity. NSAIDs with short elimination half-lives (e.g., diclofenac, indomethacin) should be avoided for a period of two days before, the day of, and two days following administration of pemetrexed. In the absence of data regarding potential interaction between pemetrexed and NSAIDs with longer half-lives (e.g., meloxicam, nabumetone), patients taking these NSAIDs should interrupt dosing for at least five days before, the day of, and two days following pemetrexed administration.

8 USE IN SPECIFIC POPULATIONS

8.1 Pregnancy

Pregnancy Category C prior to 30 weeks gestation; Category D starting 30 weeks gestation

Risk Summary

Use of NSAIDs, including VOLTAREN® GEL, during the third trimester of pregnancy increases the risk of premature closure of the fetal ductus arteriosus. Avoid use of NSAIDs, including VOLTAREN® GEL, in pregnant women starting at 30 weeks of gestation (third trimester).

There are no adequate and well-controlled studies of VOLTAREN® GEL in pregnant women. Human and animal studies indicate that diclofenac crosses the placenta. Data from observational studies regarding potential embryofetal risks of NSAID use in women in the first or second trimesters of pregnancy are inconclusive. In the general U.S. population, all clinically recognized pregnancies, regardless of drug exposure, have a background rate of 2-4% for major malformations, and 15-20% for pregnancy loss. In animal reproduction studies, no evidence of teratogenicity was observed in mice, rats, or rabbits given diclofenac during the period of organogenesis at doses up to approximately 5, 5, and 10 times, respectively, the maximum recommended topical dose of VOLTAREN® GEL, despite the presence of maternal and fetal toxicity at these doses [see Data]. Based on animal data, prostaglandins have been shown to have an important role in endometrial vascular permeability, blastocyst implantation, and decidualization. In animal studies, administration of prostaglandin synthesis inhibitors such as diclofenac, resulted in increased pre- and post-implantation loss.

Clinical Considerations

Labor or Delivery

There are no studies on the effects of VOLTAREN® GEL during labor or delivery. In animal studies, NSAIDS, including diclofenac, inhibit prostaglandin synthesis, cause delayed parturition, and increase the incidence of stillbirth.

Data

Animal data

Reproductive and developmental studies in animals demonstrated that diclofenac sodium administration during organogenesis did not produce teratogenicity despite the induction of maternal toxicity and fetal toxicity in mice at oral doses up to 20 mg/kg/day (approximately 5 times the maximum recommended human dose (MRHD) of VOLTAREN® GEL based on bioavailability and body surface area (BSA) comparison), and in rats and rabbits at oral doses up to 10 mg/kg/day (approximately 5 and 10 times the MRHD based on bioavailability and BSA comparison).

In a study in which pregnant rats were orally administered 2 or 4 mg/kg diclofenac (approximately 1 and 2 times the MRHD based on bioavailability and BSA comparison) from Gestation Day 15 through Lactation Day 21, significant maternal toxicity (peritonitis, mortality) was noted. These maternally toxic doses were associated with dystocia, prolonged gestation, reduced fetal weights and growth, and reduced fetal survival.

8.2 Lactation

Risk Summary

Based on available data, diclofenac may be present in human milk. The developmental and health benefits of breastfeeding should be considered along with the mother’s clinical need for CATAFLAM and any potential adverse effects on the breastfed infant from the CATAFLAM or from the underlying maternal condition.

Data

One woman treated orally with a diclofenac salt, 150 mg/day, had a milk diclofenac level of 100 mcg/L, equivalent to an infant dose of about 0.03 mg/kg/day. Diclofenac was not detectable in breast milk in 12 women using diclofenac (after either 100 mg/day orally for 7 days or a single 50 mg intramuscular dose administered in the immediate postpartum period).

8.3 Females and Males of Reproductive Potential

Infertility

Females

Based on the mechanism of action, the use of prostaglandin-mediated NSAIDs, including VOLTAREN® GEL, may delay or prevent rupture of ovarian follicles, which has been associated with reversible infertility in some women. Published animal studies have shown that administration of prostaglandin synthesis inhibitors has the potential to disrupt prostaglandin‑mediated follicular rupture required for ovulation. Small studies in women treated with NSAIDs have also shown a reversible delay in ovulation. Consider withdrawal of NSAIDs, including VOLTAREN® GEL, in women who have difficulties conceiving or who are undergoing investigation of infertility.

8.4 Pediatric Use

Safety and effectiveness in pediatric patients have not been established.

8.5 Geriatric Use

Elderly patients, compared to younger patients, are at greater risk for NSAID-associated serious cardiovascular, gastrointestinal, and/or renal adverse reactions. If the anticipated benefit for the elderly patient outweighs these potential risks, start dosing at the low end of the dosing range, and monitor patients for adverse effects [see Warnings and Precautions (5.1, 5.2, 5.3, 5.6, 5.13)].

Of the total number of subjects treated with VOLTAREN® GEL in clinical studies, 498 were 65 years of age and over. No overall differences in effectiveness or safety were observed between these subjects and younger subjects, but greater sensitivity to the effect of NSAIDs in some older individuals cannot be ruled out.

Diclofenac, as with any NSAID, is known to be substantially excreted by the kidney, and the risk of toxic reactions to VOLTAREN® GEL may be greater in patients with impaired renal function. Because elderly patients are more likely to have decreased renal function, care should be taken when using VOLTAREN® GEL in the elderly, and it may be useful to monitor renal function.

10 OVERDOSAGE

Symptoms following acute NSAID overdosages have been typically limited to lethargy, drowsiness, nausea, vomiting, and epigastric pain, which have been generally reversible with supportive care. Gastrointestinal bleeding has occurred. Hypertension, acute renal failure, respiratory depression, and coma have occurred, but were rare [see Warnings and Precautions (5.1, 5.2, 5.4, 5.6)].

Manage patients with symptomatic and supportive care following an NSAID overdosage. There are no specific antidotes. Forced diuresis, alkalinization of urine, hemodialysis, or hemoperfusion may not be useful due to high protein binding.

For additional information about overdosage treatment, contact a poison control center (1-800-222-1222).

11 DESCRIPTION

VOLTAREN® GEL (diclofenac sodium topical gel) is a nonsteroidal anti-inflammatory drug (NSAID) for topical use only. The chemical name is 2-[(2,6-dichlorophenyl)amino]benzene acetic acid, monosodium salt. The molecular weight is 318.14. Its molecular formula is C14H10Cl2NNaO2, and it has the following chemical structure:

It contains the active ingredient, diclofenac sodium, in an opaque, white gel base. Diclofenac sodium is a white to slightly yellow crystalline powder. Diclofenac sodium is a benzeneacetic acid derivative.

The inactive ingredients in VOLTAREN® GEL include: carbomer homopolymer Type C, cocoyl caprylocaprate, fragrance, isopropyl alcohol, mineral oil, polyoxyl 20 cetostearyl ether, propylene glycol, purified water, and strong ammonia solution.

12 CLINICAL PHARMACOLOGY

12.1 Mechanism of Action

Diclofenac has analgesic, anti-inflammatory, and antipyretic properties.

The mechanism of action of VOLTAREN® GEL, like that of other NSAIDs, is not completely understood but involves inhibition of cyclooxygenase (COX-1 and COX-2).

Diclofenac is a potent inhibitor of prostaglandin synthesis in vitro. Diclofenac concentrations reached during therapy have produced in vivo effects. Prostaglandins sensitize afferent nerves and potentiate the action of bradykinin in inducing pain in animal models. Prostaglandins are mediators of inflammation. Because diclofenac is an inhibitor of prostaglandin synthesis, its mode of action may be due to a decrease of prostaglandins in peripheral tissues.

12.3 Pharmacokinetics

The pharmacokinetics of VOLTAREN® GEL were assessed in healthy volunteers following repeated applications during 7 days of VOLTAREN® GEL to 1 knee (4 x 4 g per day) or to 2 knees and 2 hands (4 x 12 g per day) versus the recommended oral dose of diclofenac sodium for the treatment of osteoarthritis (3 x 50 mg per day). A summary of the pharmacokinetic parameters is presented in Table 2.

Table 3. Pharmacokinetic Parameters and Comparison of VOLTAREN® GEL to Oral Diclofenac Sodium Tablets After Repeated Administration

Treatment | Cmax (ng/mL) Mean ± SD % of Oral (CI) | Tmax (hr) Median Range | AUC0-24 (ng●h/mL) Mean ± SD % of Oral (CI)
VOLTAREN® GEL 4 x 4 g per day (=160 mg diclofenac sodium per day) | 15 ± 7.3 0.6% (0.5-0.7) | 14 (0-24) | 233 ± 128 5.8% (5-6.7)
VOLTAREN® GEL 4 x 12 g per day (=480 mg diclofenac sodium per day) | 53.8 ± 32 2.2% (1.9-2.6) | 10 (0-24) | 807 ± 478 19.7% (17-22.8)
Diclofenac sodium tablets, orally 3 x 50 mg per day (=150 mg diclofenac sodium per day) | 2270 ± 778 100% | 6.5 (1-14) | 3890 ± 1710 100%

Cmax = maximum plasma concentration, tmax=time of Cmax. AUC0-24=area under the concentration time curve. SD=standard deviation. CI=confidence interval.

Systemic exposure (area under the concentration-time curve) and maximum plasma concentrations of diclofenac are significantly lower with VOLTAREN® GEL than with comparable oral treatment of diclofenac sodium.

Systemic exposure with recommended use of VOLTAREN® GEL (4 x 4 g per day applied to 1 knee) is on average 17 times lower than with oral treatment. (Basis: treatment with VOLTAREN® GEL of 1 knee, 4 times a day versus 50 mg, 3 times a day of oral diclofenac tablets.) The amount of diclofenac sodium that is systemically absorbed from VOLTAREN® GEL is on average 6% of the systemic exposure from an oral form of diclofenac sodium.

The average peak plasma concentration with recommended use of VOLTAREN® GEL (4 x 4 g per day applied to 1 knee) is 158 times lower than with the oral treatment.

The pharmacokinetics of VOLTAREN® GEL has been tested under conditions of moderate heat (application of a heat patch for 15 minutes prior to gel application) and of moderate exercise (first gel application followed by a 20-minute treadmill exercise). No clinically relevant differences of systemic absorption and of tolerability were found between applications of VOLTAREN® GEL (4 x 4 g per day on 1 knee) with and under the conditions tested. However, the pharmacokinetics of VOLTAREN® GEL were not tested under the condition of heat application following gel application. Therefore, concurrent use of VOLTAREN® GEL and heat is not recommended.

Drug Interaction Studies

Aspirin: When NSAIDs were administered with aspirin, the protein binding of NSAIDs were reduced, although the clearance of free NSAID was not altered. The clinical significance of this interaction is not known. See Table 2 for clinically significant drug interactions of NSAIDs with aspirin [see Drug Interactions (7)].

13 NONCLINICAL TOXICOLOGY

13.1 Carcinogenesis, Mutagenesis, Impairment of Fertility

Carcinogenesis

Carcinogenicity studies in mice and rats administered diclofenac sodium as a dietary constituent for 2 years at doses up to 2 mg/kg/day (approximately 0.5 and 1 times, respectively, the maximum recommended human topical dose of VOLTAREN® GEL based on bioavailability and body surface area (BSA) comparison) resulted in no significant increases in tumor incidence.

In a dermal carcinogenicity study conducted in albino mice, daily topical applications of a diclofenac sodium gel product for two years at concentrations up to 0.035% diclofenac sodium (a 29-fold lower diclofenac sodium concentration than present in VOLTAREN® GEL) did not increase neoplasm incidence.

In a photococarcinogenicity study conducted in hairless mice, topical application of a diclofenac sodium gel product at doses up to 0.035% diclofenac sodium (a 29-fold lower diclofenac sodium concentration than present in VOLTAREN® GEL) resulted in an earlier median time of onset of tumors.

Mutagenesis

Diclofenac was not mutagenic or clastogenic in a battery of genotoxicity tests that included the bacterial reverse mutation assay, in vitro mouse lymphoma point mutation assay, chromosomal aberration studies in Chinese hamster ovarian cells in vitro, and in vivo rat chromosomal aberration assay of bone marrow cells.

Impairment of Fertility

Diclofenac did not affect male or female fertility in rats at doses up to 4 mg/kg/day (approximately 2 times than the maximum human topical dose of VOLTAREN® GEL based on bioavailability and BSA comparison).

14 CLINICAL STUDIES

14.1 Pivotal Studies in Osteoarthritis of the Superficial Joints of the Extremities

Study 1 evaluated the efficacy of VOLTAREN® GEL for the treatment of osteoarthritis of the knee in a 12-week, randomized, double-blind, multicenter, placebo-controlled, parallel-group trial. VOLTAREN® GEL was administered at a dose of 4 g, 4 times daily, on 1 knee (16 g per day). Pain as assessed by the patients at Week 12 using the WOMAC (Western Ontario and McMaster Universities Osteoarthritis Index) Pain Subindex was lower in the VOLTAREN® GEL group than the placebo group.

Study 2 evaluated the efficacy of VOLTAREN® GEL for the treatment of osteoarthritis in subjects with osteoarthritis of the hand in an 8-week, randomized, double-blind, multicenter, placebo-controlled, parallel-group study. VOLTAREN® GEL was administered at a dose of 2 g per hand, 4 times daily, on both hands (16 g per day). Pain in the target hand as assessed by the patients at Weeks 4 and 6 on a visual analog scale from 0 to 100 was lower in the VOLTAREN® GEL group than the placebo group.

Table 4. Efficacy outcomes of VOLTAREN® GEL in Studies 1 and 2
 |  | VOLTAREN® GEL | Placebo (Vehicle) | Adjusted Difference (Placebo - VOLTAREN® GEL)
Study 1 (Knee) WOMAC Pain * # at Week 12 | Sample Size | 127 | 119
Study 1 (Knee) WOMAC Pain * # at Week 12 | Mean Outcome | 28 | 37 | ∆ = 7†
Study 1 (Knee) WOMAC Pain * # at Week 12 | 95% Confidence Interval |  |  | (1, 12)
Study 2 (Hand) Pain Intensity # at Week 4 | Sample Size | 198 | 187
Study 2 (Hand) Pain Intensity # at Week 4 | Mean Outcome | 43 | 50 | ∆ = 7 ‡
Study 2 (Hand) Pain Intensity # at Week 4 | 95% Confidence Interval |  |  | (2, 12)
Study 2 (Hand) Pain Intensity # at Week 6 | Sample Size | 198 | 187
Study 2 (Hand) Pain Intensity # at Week 6 | Mean Outcome | 40 | 47 | ∆ = 7 ‡
Study 2 (Hand) Pain Intensity # at Week 6 | 95% Confidence Interval |  |  | (1, 13)

* WOMAC = Western Ontario McMaster Osteoarthritis Index.

# Scale from 0 (best) to 100 (worst).

† Difference is adjusted using an analysis of covariance (ANCOVA) model with main effects of treatment and center and baseline covariate.

‡ Difference is adjusted using an analysis of covariance (ANCOVA) model with main effects of treatment, center, indicator of pain in the CMC-1 joint, and baseline as a covariate, and the treatment-by-CMC-1 strata.

16 HOW SUPPLIED/STORAGE AND HANDLING

Product: 50436-3621

NDC: 50436-3621-1 100 g in a TUBE

17 PATIENT COUNSELING INFORMATION

Advise the patient to read the FDA-approved patient labeling (Medication Guide and Instructions for Use) that accompanies each prescription dispensed. Patients, families, or their caregivers should be informed of the following information before initiating therapy with VOLTAREN® GEL and periodically during the course of ongoing therapy.

Cardiovascular Thrombotic Events

Advise patients to be alert for the symptoms of cardiovascular thrombotic events, including chest pain, shortness of breath, weakness, or slurring of speech, and to report any of these symptoms to their health care provider immediately [see Warnings and Precautions (5.1)].

Gastrointestinal Bleeding, Ulceration, and Perforation

Advise patients to report symptoms of ulcerations and bleeding, including epigastric pain, dyspepsia, melena, and hematemesis to their health care provider. In the setting of concomitant use of low-dose aspirin for cardiac prophylaxis, inform patients of the increased risk for and the signs and symptoms of GI bleeding [see Warnings and Precautions (5.2)].

Hepatotoxicity

Inform patients of the warning signs and symptoms of hepatotoxicity (e.g., nausea, fatigue, lethargy, pruritus, diarrhea, jaundice, right upper quadrant tenderness, and “flu-like” symptoms). If these occur, instruct patients to stop VOLTAREN® GEL and seek immediate medical therapy [see Warnings and Precautions (5.3)].

Heart Failure and Edema

Advise patients to be alert for the symptoms of congestive heart failure including shortness of breath, unexplained weight gain, or edema and to contact their healthcare provider if such symptoms occur [see Warnings and Precautions (5.5)].

Anaphylactic Reactions

Inform patients of the signs of an anaphylactic reaction (e.g., difficulty breathing, swelling of the face or throat). Instruct patients to seek immediate emergency help if these occur [see Contraindications (4) and Warnings and Precautions (5.7)].

Serious Skin Reactions

Advise patients to stop VOLTAREN® GEL immediately if they develop any type of rash and to contact their healthcare provider as soon as possible [see Warnings and Precautions (5.9)].

Female Fertility

Advise females of reproductive potential who desire pregnancy that NSAIDs, including VOLTAREN® GEL, may be associated with a reversible delay in ovulation [see Use in Specific Populations (8.3)]

Fetal Toxicity

Inform pregnant women to avoid use of VOLTAREN® GEL and other NSAIDs starting at 30 weeks gestation because of the risk of the premature closing of the fetal ductus arteriosus [see Warnings and Precautions (5.10) and Use in Specific Populations (8.1)].

Avoid Concomitant Use of NSAIDs

Inform patients that the concomitant use of VOLTAREN® GEL with other NSAIDs or salicylates (e.g., diflunisal, salsalate) is not recommended due to the increased risk of gastrointestinal toxicity, and little or no increase in efficacy [see Warnings and Precautions (5.2) and Drug Interactions (7)]. Alert patients that NSAIDs may be present in "over the counter" medications for treatment of colds, fever, or insomnia.

Use of NSAIDS and Low-Dose Aspirin

Inform patients not to use low-dose aspirin concomitantly with VOLTAREN® GEL until they talk to their healthcare provider [see Drug Interactions (7)].

Eye Exposure

Instruct patients to avoid contact of VOLTAREN® GEL with the eyes and mucosa, although not studied, should be avoided. Advise patients that if eye contact occurs, immediately wash out the eye with water or saline and consult a physician if irritation persists for more than an hour [see Warnings and Precautions (5.15)].

Special Application Instructions

Instruct patients how to use the dosing card to measure the proper dose of VOLTAREN® GEL to apply.
If the patient loses their dosing card, instruct them that they can call 1-800-398-5876 to request a replacement dosing card or ask their pharmacist for a new dosing card.

Instruct patients how to correctly measure the 2.25 inches (2 g) dose or 4.5 inches (4 g) dose while waiting for a replacement dosing card [see Dosage and Administration (2.2)].

Instruct patients not to apply VOLTAREN® GEL to open skin wounds, infections, inflammations, or exfoliative dermatitis, as it may affect absorption and tolerability of the drug.

Instruct patients to avoid concomitant use of VOLTAREN® GEL with other topical products, including sunscreens, cosmetics, lotions, moisturizers, and insect repellants. Concomitant use may result in skin reactions or change the absorption of VOLTAREN® GEL.

Instruct patients to minimize or avoid exposure of treated areas to natural or artificial sunlight [see Warnings and Precautions (5.14) and Dosage and Administration (2.4)].

Comments or Questions?

Call toll-free 1-800-398-5876

Marketed by:

Endo Pharmaceuticals Inc.

Malvern, PA 19355

Manufactured by:

Novartis Pharma Produktions GmbH,

Wehr, Germany for

Sandoz Inc., Princeton, NJ 08540

Revised: April 2016

Medication Guide

Medication Guide for Nonsteroidal Anti-Inflammatory Drugs (NSAIDs)

What is the most important information I should know about medicines called Nonsteroidal Anti-Inflammatory Drugs (NSAIDs)?

NSAIDs can cause serious side effects, including:

- Increased risk of a heart attack or stroke that can lead to death. This risk may happen early in treatment and may increase:
  - with increasing doses of NSAIDs
  - with longer use of NSAIDs

Do not take NSAIDs right before or after a heart surgery called a “coronary artery bypass graft (CABG).”

Avoid taking NSAIDs after a recent heart attack, unless your healthcare provider tells you to. You may have an increased risk of another heart attack if you take NSAIDs after a recent heart attack.

- Increased risk of bleeding, ulcers, and tears (perforation) of the esophagus (tube leading from the mouth to the stomach), stomach and intestines:
  - anytime during use
  - without warning symptoms
  - that may cause death

The risk of getting an ulcer or bleeding increases with:

  - past history of stomach ulcers, or stomach or intestinal bleeding with use of NSAIDs
  - taking medicines called “corticosteroids”, “anticoagulants”, “SSRIs”, or “SNRIs
  - increasing doses of NSAIDs
  - older age
  - longer use of NSAID
  - poor health
  - smoking
  - advanced liver problems
  - drinking alcohol
  - bleeding problems

NSAIDs should only be used:

  - exactly as prescribed
  - at the lowest dose possible for your treatment
  - for the shortest time needed

What are NSAIDs?

NSAIDs are used to treat pain and redness, swelling, and heat (inflammation) from medical conditions such as different types of arthritis, menstrual cramps, and other types of short-term pain

Who should not take NSAIDs?

Do not take NSAIDs :

- if you had an asthma attack, hives, or other allergic reaction with aspirin or any other NSAIDs
- right before or after heart bypass surgery

Before taking NSAIDs, tell your healthcare provider about all of your medical conditions, including if you:

- have liver or kidney problems
- have high blood pressure
- have asthma
- are pregnant or plan to become pregnant. Talk to your healthcare provider if you are considering taking NSAIDs during pregnancy. You should not take NSAIDs after 29 weeks of pregnancy.
- Are breastfeeding or plan to breast feed

Tell your healthcare provider all of the medicines you take, including prescription or over-the-counter medicines, vitamins or herbal supplements. NSAIDs and some other medicines can interact with each other and cause serious side effects. Do not start taking any new medicine without talking to your healthcare provider first.

What are the possible side effects of NSAIDs?

NSAIDs can cause serious side effects, including:

See “What is the most important information I should know about medicines called Nonsteroidal Anti-inflammatory Drugs (NSAIDs)?”

- new or worse high blood pressure
- heart failure
- liver problems including liver failure
- kidney problems including kidney failure
- low red blood cells (anemia)
- life-threatening skin reactions
- life-threatening allergic reactions
- Other side effects of NSAIDs include: stomach pain, constipation, diarrhea, gas, heartburn, nausea, vomiting, and dizziness.

Get emergency help right away if you have any of the following symptoms:

- shortness of breath or trouble breathing
- slurred speech
- chest pain
- swelling of the face or throat
- weakness in one part or side of your body

Stop taking your NSAID and call your healthcare provider right away if you get any of the following symptoms:

- nausea
- vomit blood
- more tired or weaker than usual
- there is blood in your bowel movement or it is black and sticky like tar
- diarrhea
- itching
- unusual weight gain
- your skin or eyes look yellow
- skin rash or blisters with fever
- indigestion or stomach pain
- swelling of the arms, legs, hands and feet
- flu-like symptoms

If you take too much of your NSAID, call your healthcare provider or get medical help right away.

These are not all the possible side effects of NSAIDs. For more information, ask your healthcare provider or pharmacist about NSAIDs.

Call your doctor for medical advice about side effects. You may report side effects to FDA at 1-800-FDA-1088.

Other information about NSAIDs

- Aspirin is an NSAID but it does not increase the chance of a heart attack. Aspirin can cause bleeding in the brain, stomach, and intestines. Aspirin can also cause ulcers in the stomach and intestines.
- Some NSAIDs are sold in lower doses without a prescription (over-the-counter). Talk to your healthcare provider before using over-the-counter NSAIDs for more than 10 days.

General Information about the safe and effective use of NSAIDs

Medicines are sometimes prescribed for purposes other than those listed in a Medication Guide. Do not use NSAIDs for a condition for which it was not prescribed. Do not give NSAIDs to other people, even if they have the same symptoms that you have. It may harm them.

If you would like more information about NSAIDs, talk with your healthcare provider. You can ask your pharmacist or healthcare provider for information about NSAIDs that is written for health professionals.

This Medication Guide has been approved by the U.S. Food and Drug Administration.

Marketed by:

Endo Pharmaceuticals Inc., Malvern, PA 19355

Manufactured by:

Novartis Pharma Produktions GmbH,

Wehr, Germany for

Sandoz Inc., Princeton, NJ 08540

Revised: April 2016

Instructions for Use

VOLTAREN® GEL (diclofenac sodium)

Important: Use the dosing card that is inside the VOLTAREN® GEL carton to correctly measure each dose. The dosing card is re-usable. Do not throw the dosing card away. Before you use VOLTAREN® GEL for the first time, your healthcare provider or pharmacist should show you how to correctly measure your dose using the dosing card.

Read this Instructions for Use before you start using VOLTAREN® GEL and each time you get a refill. There may be new information. This information does not take the place of talking to your healthcare provider about your medical condition or your treatment.

Your healthcare provider has prescribed VOLTAREN® GEL to help relieve arthritis pain in some of your joints. VOLTAREN® GEL may be used to treat arthritis pain in the arms (hands, wrists, and elbows) and in the legs (feet, ankles, and knees). It is not known if VOLTAREN® GEL is safe and effective if used on your spine, hips, or shoulders.

- Use VOLTAREN® GEL exactly how your healthcare provider prescribes it for you. Do not apply VOLTAREN® GEL anywhere other than where your healthcare provider tells you to.
- Do not use more than a total of 32 grams of VOLTAREN® GEL each day. If you add up the amount of VOLTAREN® GEL as directed by your healthcare provider, it should not be more than 32 grams in one day.

The dose for your hands, wrists, or elbows is 2 grams of VOLTAREN® GEL each time you apply it.

- Apply VOLTAREN® GEL 4 times a day (a total of 8 grams each day). Do not apply more than 8 grams each day to any one of your affected hands, wrists, or elbows.

The dose for your feet, ankles, or knees is 4 grams of VOLTAREN® GEL each time you apply it.

- Apply VOLTAREN® GEL 4 times a day (a total of 16 grams each day). Do not apply more than 16 grams each day to any one of your affected feet, ankles, or knees.

Some examples of VOLTAREN® GEL application include:

- If you use 2 grams of VOLTAREN® GEL on one hand, 4 times a day, your total dose for one day is 8 grams.
- If you use 4 grams of VOLTAREN® GEL on one knee, 4 times a day, your total dose for one day is 16 grams.
- Your total dose for one day, treating one hand and one knee, is 8 grams plus 16 grams, which equals 24 grams of VOLTAREN® GEL.

- Before you use a new tube of VOLTAREN® GEL for the first time, open the foil seal that covers the tube opening by using the spiked top of the cap. Remember to remove the dosing card from the carton to measure your dose (see Figure A).
- Apply VOLTAREN® GEL to clean, dry skin that does not have any cuts, open wounds, infections, or rashes.
- Do not use heating pads or apply bandages to where you have applied VOLTAREN® GEL.
- Avoid exposing skin where you apply VOLTAREN® GEL to sunlight and artificial light, such as tanning booths.
- Do not use sunscreens, cosmetics, lotions, moisturizers, insect repellants, or other topical medicines on the same skin areas where you have applied VOLTAREN® GEL.
- Do not get VOLTAREN® GEL in your eyes, nose, or mouth. VOLTAREN® GEL is only to be used on your skin (topical use). If you get VOLTAREN® GEL in your eyes, rinse your eyes right away with water or saline. Talk with your healthcare provider if eye irritation lasts for more than one hour.

What if I miss a dose?

- If you miss a dose of VOLTAREN® GEL, continue with your next scheduled dose using the prescribed amount of VOLTAREN® GEL. Do not double the dose.

Applying 2 grams (2 g) of VOLTAREN® GEL to hands, wrists, or elbows:

Step 1. Remove the dosing card that is attached inside the VOLTAREN® GEL carton. Use the dosing card to correctly measure each dose of VOLTAREN® GEL. To measure the correct amount of VOLTAREN® GEL, place the dosing card on a flat surface so that you can read the print. If the print is backwards, flip dosing card over (see Figure A). If you lose or misplace your dosing card, you can ask your pharmacist for a new one or call 1-800-452-0051. Ask your healthcare provider or pharmacist to show you how to correctly measure your dose of VOLTAREN® GEL while you are waiting to receive your new dosing card.

Step 2. Squeeze VOLTAREN® GEL onto the dosing card evenly, up to the 2 g line (a 2.25 inch length of gel). Make sure that the gel covers the 2 g area of the dosing card (see Figure B). Put the cap back on the tube of VOLTAREN® GEL. Ask your healthcare provider or pharmacist if you are not sure how to correctly measure your dose of VOLTAREN® GEL.

Step 3. Apply the gel to your hand, wrist, or elbow. You can use the dosing card to apply the gel (see Figure C). Then, use your hands to gently rub the gel into the skin (see Figure D). Do not share your dosing card with another person. Make sure to cover the entire affected hand, wrist, or elbow with the gel. Remember that the hand includes the palm of your hand, the top of your hand, and your fingers.

Step 4. After using the dosing card, hold end with fingertips, rinse and dry. Store the dosing card until next use. Do not shower or bathe for at least 1 hour after applying VOLTAREN® GEL. Do not wash your treated hands for at least 1 hour after applying the VOLTAREN® GEL.

Step 5. After applying VOLTAREN® GEL, wait 10 minutes before covering the treated skin with gloves or clothing.

Applying 4 grams (4 g) of VOLTAREN® GEL to feet, ankles, or knees:

Step 1. Refer to Step 1 above.

Step 2. Squeeze VOLTAREN® GEL onto the dosing card evenly up to the 4 g line (a 4.5 inch length of gel), making sure the gel covers the 4 g area of the dosing card (see Figure E). Put the cap back on the tube of VOLTAREN® GEL. Ask your healthcare provider or pharmacist if you are not sure how to correctly measure your dose of VOLTAREN® GEL.

Step 3. Apply VOLTAREN® GEL to your foot, ankle, or knee. You can use the dosing card to apply the gel (see Figure F). Then, use your hands to gently rub the gel into the skin (see Figure G). Do not share your dosing card with another person. Make sure to cover your entire foot, ankle, or knee area with the gel. For example, cover the skin above, below, inside and outside the knee cap. Remember that the foot includes the sole of your foot, the top of your foot, and your toes.

Refer to Steps 4 and 5 above. Wash your hands after applying VOLTAREN® GEL to your foot, ankle, or knee.

What are the ingredients in VOLTAREN® GEL?
Active ingredient: diclofenac sodium

Inactive ingredients: carbomer homopolymer Type C, cocoyl caprylocaprate, fragrance, isopropyl alcohol, mineral oil, polyoxyl 20 cetostearyl ether, propylene glycol, purified water, and strong ammonia solution.

How should I store VOLTAREN® GEL? Store at 20°C to 25°C (68°F to 77°F). Do not freeze VOLTAREN® GEL. Store the dosing card with your VOLTAREN® GEL.

Keep VOLTAREN® GEL, the dosing card, and all medicines out of the reach of children.

This Medication Guide and Instructions for Use have been approved by the U.S. Food and Drug Administration.

Marketed by:

Endo Pharmaceuticals Inc., Malvern, PA 19355

Manufactured by:

Novartis Pharma Produktions GmbH,

Wehr, Germany for

Sandoz Inc., Princeton, NJ 08540

Revised: April 2016